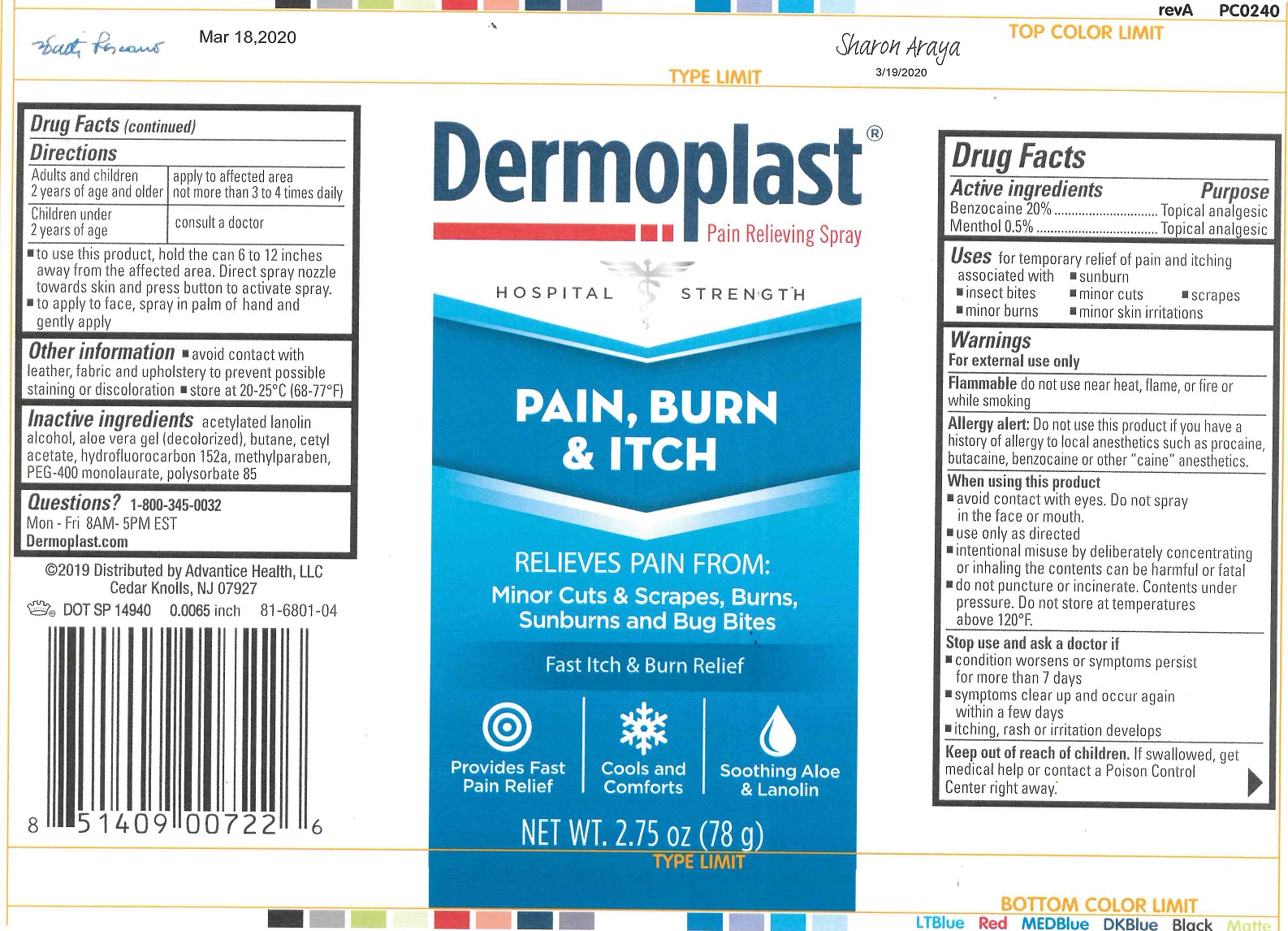 DRUG LABEL: Dermoplast Pain relieving
NDC: 16864-690 | Form: SPRAY
Manufacturer: Advantice Health
Category: otc | Type: HUMAN OTC DRUG LABEL
Date: 20231221

ACTIVE INGREDIENTS: BENZOCAINE 200 mg/1 g; MENTHOL 5 mg/1 g
INACTIVE INGREDIENTS: ALOE VERA LEAF; BUTANE; CETYL ACETATE; 1,1-DIFLUOROETHANE; METHYLPARABEN; POLYSORBATE 85

Dermoplast Pain relieving Spray

Active ingredients

Benzocaine 20%

Menthol 0.5%

Purpose

Topical analgesic

Uses

for temporary relief of pain and itching associated with • sunburn • insect bites • minor cuts • minor burns • minor skin irritations

Warnings

For external use only

do not use near heat, flame, or fire or while smoking Flammable

Do not use this product if you have a history of allergy to local anesthetics such as procaine, butacaine, benzocaine or other "caine" anesthetics. Allergy alert:

When using this product

- avoid contact with eyes. Do not spray in the face of mouth.
- use only as directed
- intentional misuse by deliberately concentrating or inhaling the contents can be harmful or fatal
- do not puncture or incinerate. Contents under pressure. Do not store at temperatures above 120°F.

Stop use and ask a doctor if

- condition worsens or symptoms persist for more than 7 days
- symptoms clear up and occur again within a few days
- itching, rash or irritation develops

Keep out of reach of children.

If swallowed, get medical help or contact a Poison Control Center right away.

Directions

Adults and children 2 years of age and older | apply to affected area not more than 3 to 4 times daily
Children under 2 years of age | consult a doctor

- to use this product, hold the can 6 to 12 inches away from the affected area. Direct spray nozzle towards skin and press button to activate spray.
- to apply to face, spray in palm of hand and gently apply

Other information

- avoid contact with leather, fabric and upholstery to prevent possible staining or discoloration
- store at 20-25°C (68-77°F)

Inactive ingredients

acetylated lanoline alcohol, aloe vera gel (decolorized), butane, cetyl acetate, hydrofluorocarbon 152a, methylparaben, PEG-400 monolaurate, polysorbate 85

Questions?

Mon - Fri 8AM- 5PM EST 1-800-345-0032 Dermoplast.com